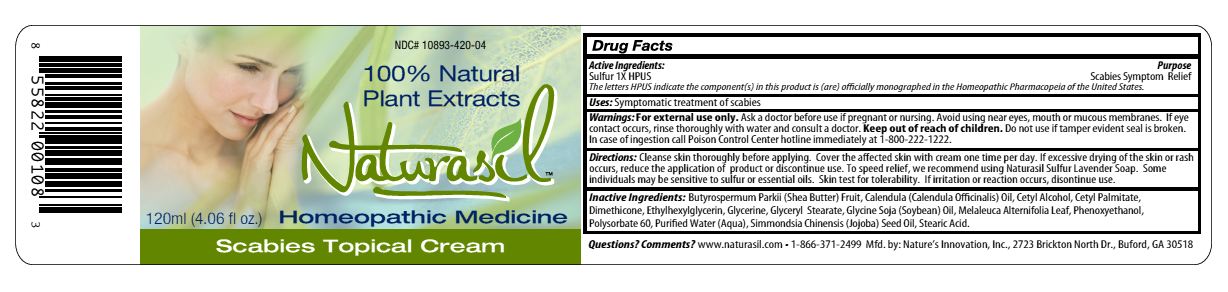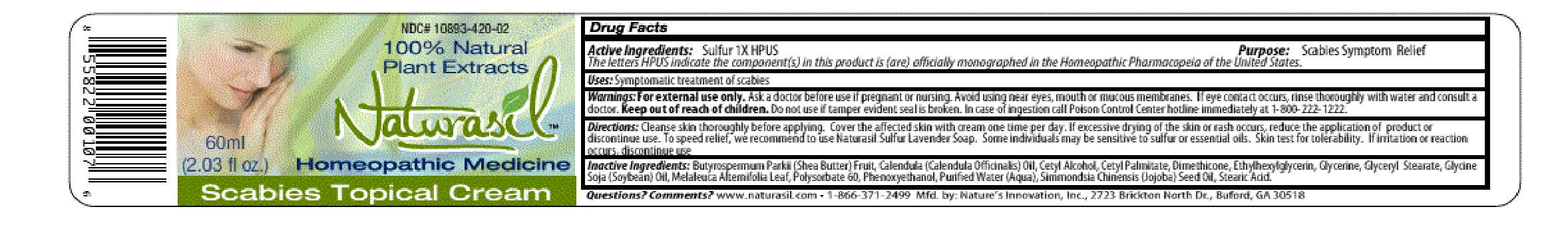 DRUG LABEL: Naturasil
NDC: 10893-420 | Form: CREAM
Manufacturer: Nature's Innovation, Inc.
Category: homeopathic | Type: HUMAN OTC DRUG LABEL
Date: 20210114

ACTIVE INGREDIENTS: SULFUR 1 [hp_X]/1 mL
INACTIVE INGREDIENTS: SHEA BUTTER; CALENDULA OFFICINALIS FLOWER; CETYL ALCOHOL; CETYL PALMITATE; DIMETHICONE; ETHYLHEXYLGLYCERIN; GLYCERIN; GLYCERYL MONOSTEARATE; SOYBEAN OIL; MELALEUCA ALTERNIFOLIA LEAF; POLYSORBATE 20; PHENOXYETHANOL; WATER; JOJOBA OIL; STEARIC ACID

Scabies Topical Cream Label

Drug Facts

Active Ingredients: Sulfur 1X HPUS

DESCRIPTION

The letters HPUS indicate the component(s) in this product is (are) officially monographed in the Homeopathic Pharmacopeia of the United States.

Purpose: Scabies Symptom Relief

INDICATIONS AND USAGE

Uses: Symptomatic treatment of scabies

Warnings: For external use only.

Ask a doctor before use if pregnant or nursing.

OTHER SAFETY INFORMATION

Avoid using near eyes, mouth or mucous membranes. If eye contact occurs, rinse thoroughly with water and consult a doctor.

Keep out of reach of children.

Do not use if tamper evident seal is broken.

OTHER SAFETY INFORMATION

In case of ingestion call Poison Control Center hotline immediately at 1-800-222-1222.

DOSAGE AND ADMINISTRATION

Directions: Cleanse skin thoroughly before applying. Cover the affected area with cream one time per day. If excessive drying of the skin or rash occurs, reduce the application of product or discontinue use. To speed relief, we recommend to use Naturasil Sulfur Lavender Soap. Some individuals may be senstive to sulfur or essential oils. Skin test for tolerability. If irritation or reaction occurs, discontinue use.

INACTIVE INGREDIENT

Inactive Ingredients: Butyrospermum Parkii (Shea Butter) Fruit, Calendula (Calendula Officinalis) Oil, Cetyl Alcohol, Cetyl Palmitate, Dimethicone, Ethylhexylglycerin, Glycerine, Glyceryl Stearate, Glycine Soja (Soybean) Oil, Melaleuca Alternifolia Leaf, Polysorbate 60, Phenoxyethanol, Purified Water (Aqua), Simmondsia Chinensis (Jojoba) Seed Oil, Stearic Acid.

QUESTIONS

Questions? Comments? www.naturasil.com 1-866-371-2499 Mfd. by: Nature's Innovation, Inc. 2723 Brickton North Dr., Buford, GA 30518

PACKAGE LABEL

NDC# 10893-420-_

100% Natural

Plant Extracts

Naturasil

__ml

(__ fl. oz.) Homeopathic Medicine

Scabies Topical Cream